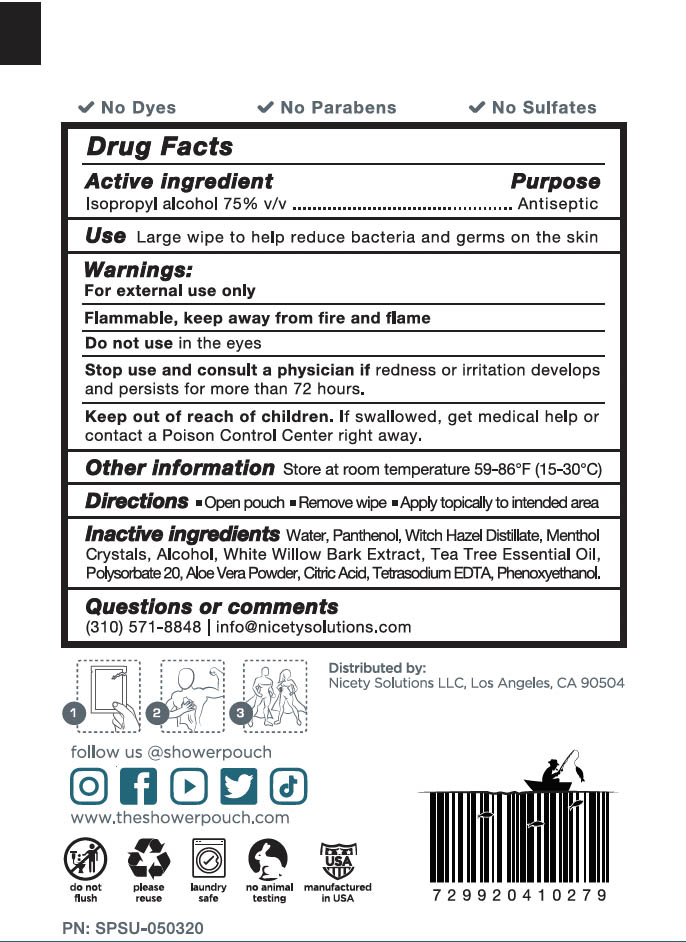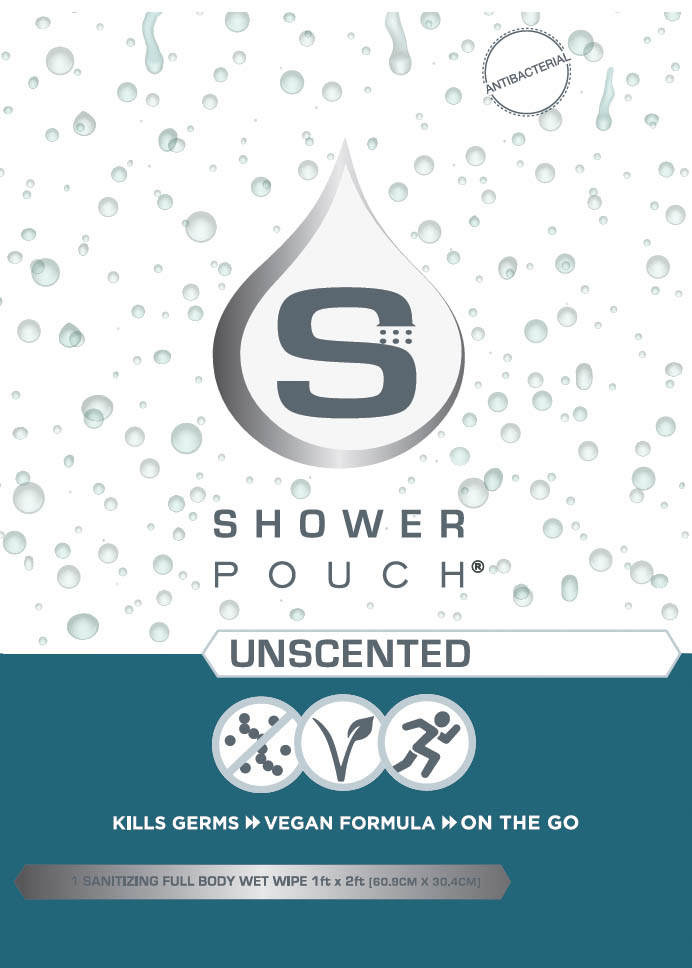 DRUG LABEL: Shower Pouch Unscented
NDC: 77371-010 | Form: CLOTH
Manufacturer: NICETY SOLUTIONS LLC
Category: otc | Type: HUMAN OTC DRUG LABEL
Date: 20220720

ACTIVE INGREDIENTS: ISOPROPYL ALCOHOL 0.75 mL/1 mL
INACTIVE INGREDIENTS: ALCOHOL; ANHYDROUS CITRIC ACID; TEA TREE OIL; MENTHOL; WILLOW BARK; PANTHENOL; WITCH HAZEL; POLYSORBATE 20; WATER; ALOE VERA LEAF; TRIMETHYLENEDIAMINETETRAACETIC ACID; PHENOXYETHANOL

Shower Pouch Unscented

Active ingredient

Isopropyl Alcohol 75% v/v

Purpose

Antiseptic

Use

Large wipe to help reduce bacteria on the skin

Warnings

For external use only

Flammable, keep away from fire and flame

Do not use

in the eyes

Keep out of reach of children

If swallowed, get medical help or contact an Poison Control Center right away.

Stop use and ask a doctor if

redness or irritation develops and persists for more than 72 hours

Other information

Store at room temperature 59-86ºF (15-30ºC)

Directions

- Open pouch
- Remove WIpe
- Apply topically to intended area

Inactive ingredients

Water, Polysorbate 20, Panthenol, Witch Hazel Distillate, Menthol Crystals, Alcohol, White Willow Bark Extract, Tea Tree Essential Oil, Aloe Vera Powder, Citric Acid, Tetrasodium EDTA, Phenoxyethanol

Questions or comments

(310) 571-8848 | Info@nicetysolutions.com

Label

Shower Pouch®

Antibacterial

Unscented

Kills Germs, Vegan Formula, On The Go

1 Sanitizing Full Body Wet Wipe 1ft x 2 ft (60.9cm x 30.4cm)